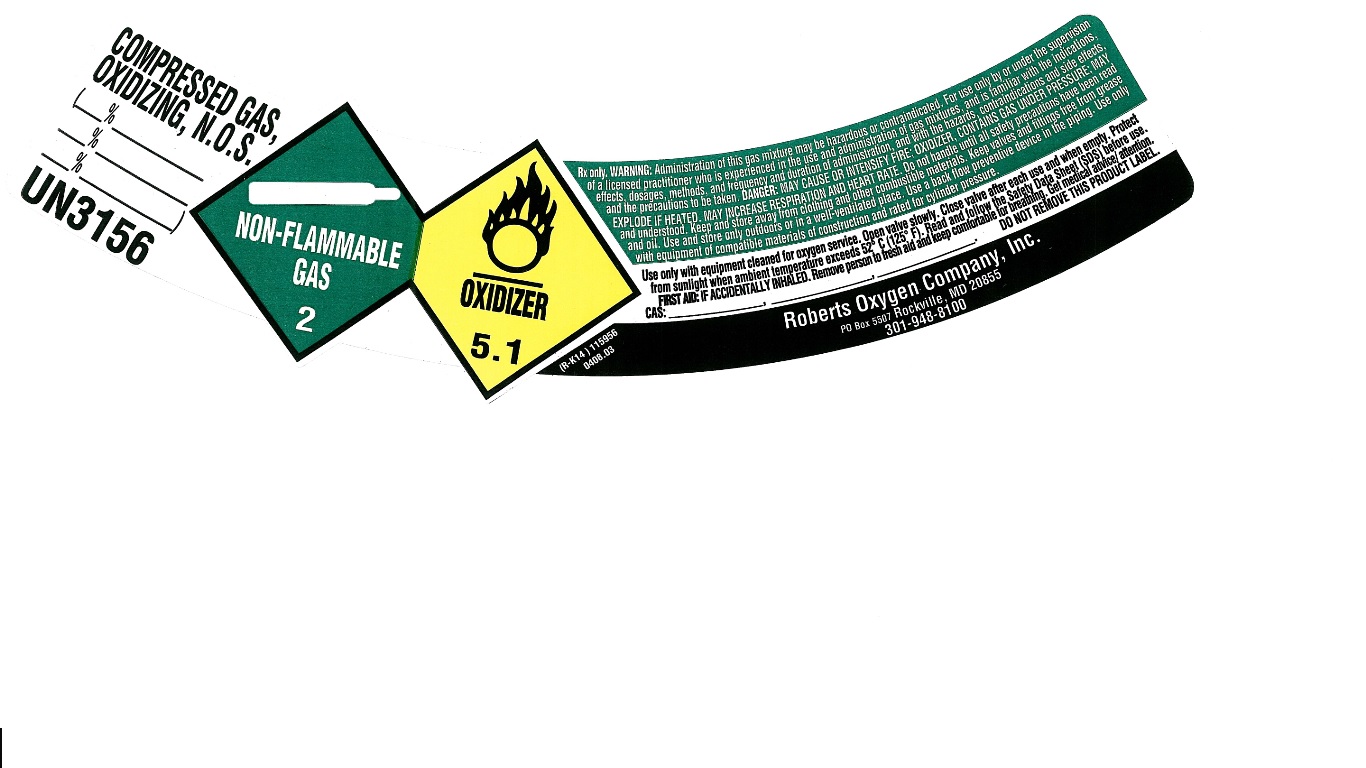 DRUG LABEL: Carbon Dioxide-Oxygen Mixture
NDC: 46123-120 | Form: GAS
Manufacturer: Roberts Oxygen Company, Inc.
Category: prescription | Type: HUMAN PRESCRIPTION DRUG LABEL
Date: 20251117

ACTIVE INGREDIENTS: CARBON DIOXIDE 70 mL/1 L; OXYGEN 930 mL/1 L

Carbon Dioxide-Oxygen Mixture -120

PACKAGE LABEL

COMPRESSED GAS, OXIDIZING, N.O.S. (%%%)
UN3156
Rx only. WARNING: Administration of this gas mixture may be hazardous or contraindicated. For use only by or under the supervision of a licensed practitioner who is experienced in the use and administration of gas mixtures, and is familiar with the indications, effects, dosages, methods, and frequency and duration of administration, and with the hazards, contraindications and side effects, and the precautions to be taken. DANGER: MAY CAUSE OR INTENSIFY FIRE; OXIDIZER, CONTAINS GAS UNDER PRESSURE; MAY EXPLODE IF HEATED. Do not handle until all safety precautions have been read and understood. Keep and store away from clothing and other combustible materials. Keep valves and fittings free from grease and oil. Use and store only outdoors or in a well-ventilated place. Use a back flow preventive device in the piping. Use only with equipment of compatible materials of construction and rated for cylinder pressure.
Use only with equipment cleaned for oxygen service. Open valve slowly. Close valve after each use and when empty. Protect from sunlight when ambient temperature exceeds 52 C (125 F). Read and follow the Safety Data Sheet (SDS) before use. FIRST AID: IF ACCIDENTALLY INHALED. Remove person to fresh air and keep comfortable for breathing. Get medical advice/attention.
CAS: ,,,. DO NOT REMOVE THIS PRODUCT LABEL.
Roberts Oxygen Company, Inc.
PO Box 5507 Rockville, MD 20855
301-948-8100